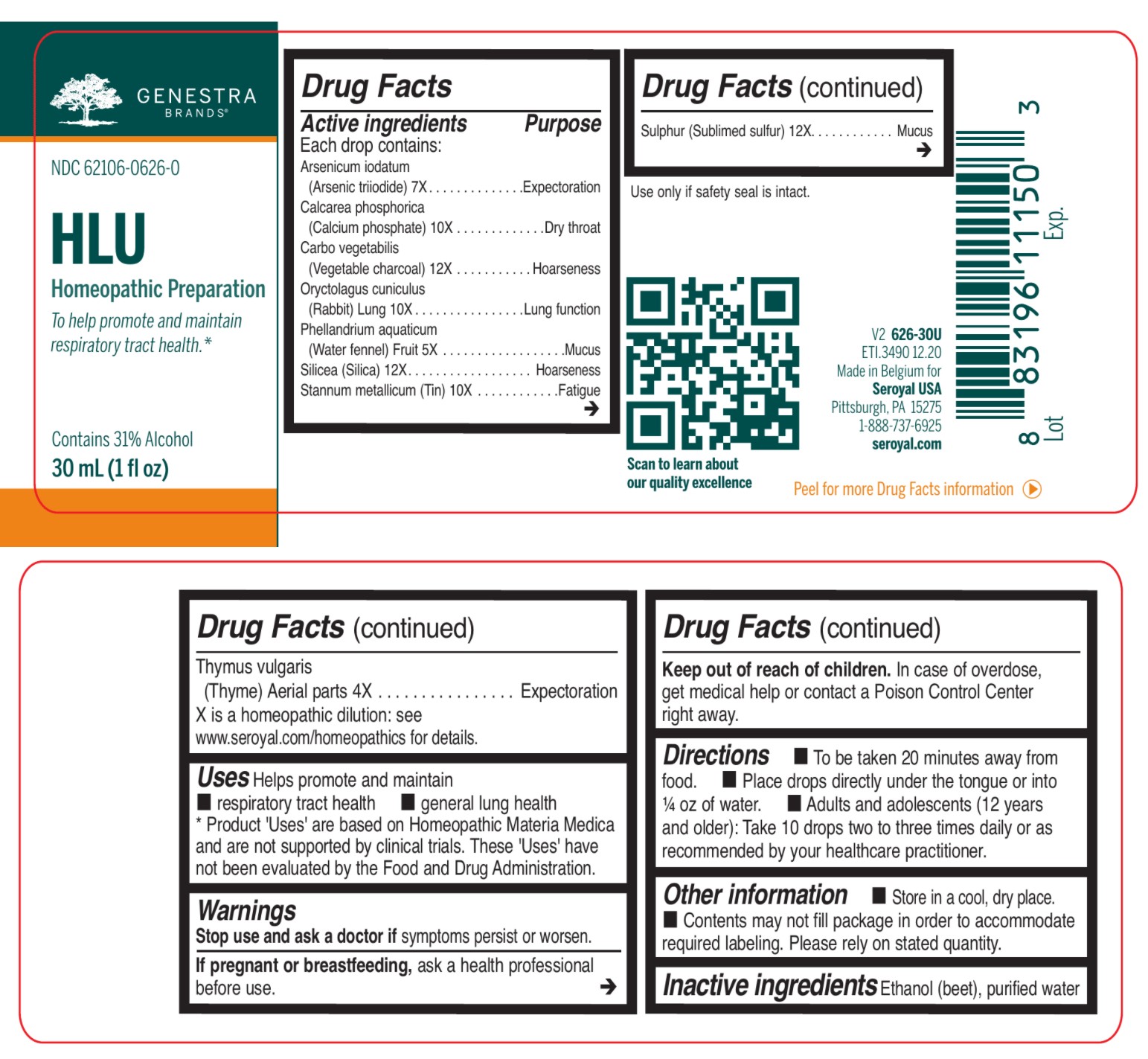 DRUG LABEL: HLU PNEUMO DROPS
NDC: 62106-0626 | Form: LIQUID
Manufacturer: Seroyal USA
Category: homeopathic | Type: HUMAN OTC DRUG LABEL
Date: 20210722

ACTIVE INGREDIENTS: SILICON DIOXIDE 12 [hp_X]/30 mL; TIN 10 [hp_X]/30 mL; SULFUR 12 [hp_X]/30 mL; TRIBASIC CALCIUM PHOSPHATE 10 [hp_X]/30 mL; ARSENIC TRIIODIDE 7 [hp_X]/30 mL; ACTIVATED CHARCOAL 12 [hp_X]/30 mL; ORYCTOLAGUS CUNICULUS LUNG 10 [hp_X]/30 mL; OENANTHE AQUATICA FRUIT 5 [hp_X]/30 mL; THYME 4 [hp_X]/30 mL
INACTIVE INGREDIENTS: ALCOHOL; WATER

HLU PNEUMO DROPS

Active ingredients

Each drop contains:
Arsenicum iodatum (Arsenic triiodide) 7X
Calcarea phosphorica (Calcium phosphate) 10X
Carbo vegetabilis (Vegetable charcoal) 12X
Oryctolagus cuniculus (Rabbit) Lung 10X
Phellandrium aquaticum (Water fennel) Fruit 5X
Silicea (Silica) 12X
Stannum metallicum (Tin) 10X
Sulphur (Sublimed sulfur) 12X

Thymus vulgaris (Thyme) Aerial Parts 4X

Uses

Helps promote and maintain respiratory tract health and general lung health

Warnings
Stop use and ask a doctor if symptoms persist or worsen.
If pregnant or breastfeeding, ask a health professional before use.
Keep out of reach of children.

In case of overdose, get medical help or contact a Poison Control Center right away.

Keep out of reach of children.

PREGNANCY OR BREAST FEEDING

If pregnant or breastfeeding, ask a health professional before use.

Other information

Store in a cool, dry place.

Contents may not fill package in order to accommodate required labeling. Please rely on stated quantity.

Inactive ingredients

Ethanol (beet), purified water

Use only if safety seal is intact.

Directions
To be taken 20 minutes away from food.

Placedrops directly under the tongue or into ¼ oz of water.

Adults and adolescents (12 years and older): Take 10 drops two to three times daily or as recommended
by your healthcare practitioner.

Children (under 12 years): Take under the direction of your healthcare practitioner.

Uses

Helps promote and maintain respiratory tract health and general lung health.

Directions
To be taken 20 minutes away from food.

Place drops directly under the tongue or into ¼ oz of water.
Adults and adolescents (12 years and older): Take 10 drops two to three times daily or as recommended
by your healthcare practitioner.

Children (under 12 years): Take under the direction of your healthcare practitioner.

PACKAGE LABEL

GENESTRA BRANDS

NDC 62106-0626-0

HLU

HOMEOPATHIC PREPARATION

To help promote and maintain
respiratory tract health.

Contains 31% Alcohol

1 fl oz (30 mL)